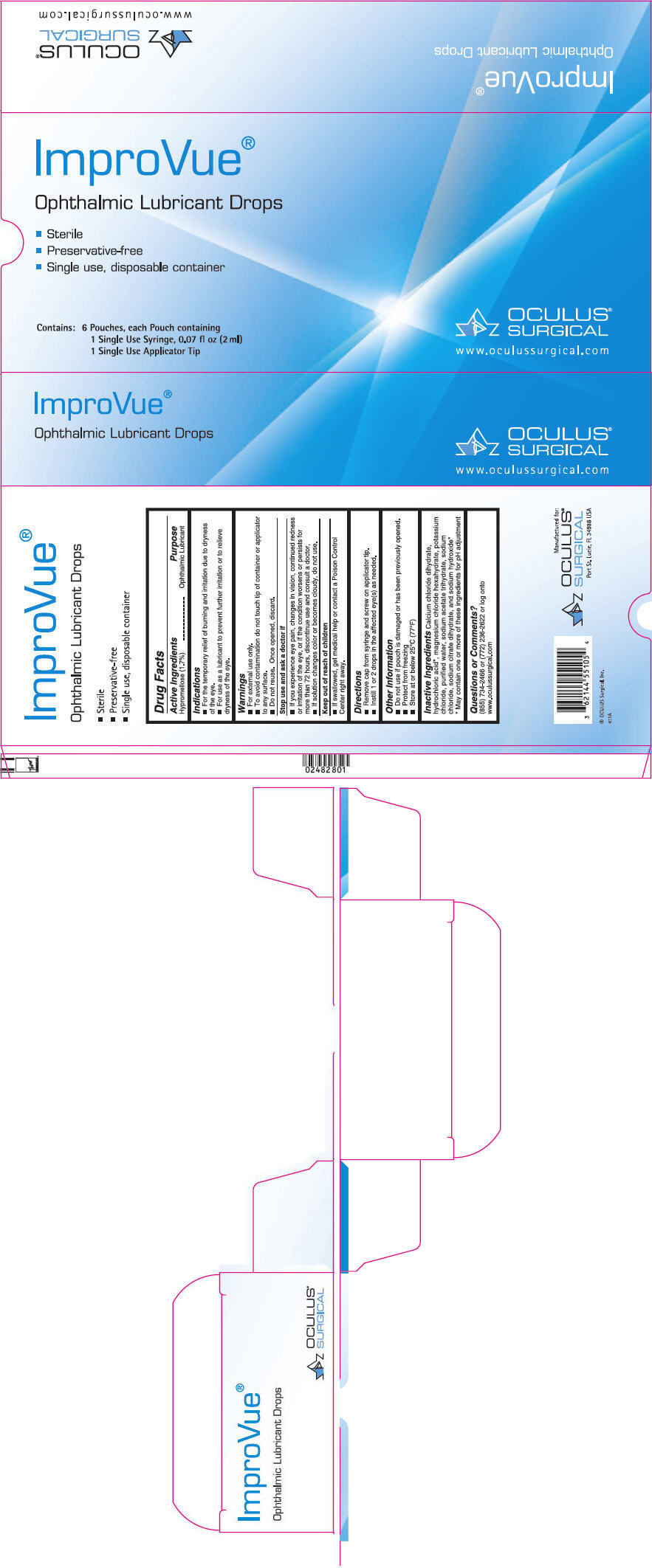 DRUG LABEL: ImproVue
NDC: 62144-5510 | Form: SOLUTION/ DROPS
Manufacturer: Oculus Surgical, Inc.
Category: otc | Type: HUMAN OTC DRUG LABEL
Date: 20250122

ACTIVE INGREDIENTS: HYPROMELLOSE 2208 (15000 MPA.S) 17 mg/1 mL
INACTIVE INGREDIENTS: CALCIUM CHLORIDE; HYDROCHLORIC ACID; MAGNESIUM CHLORIDE; POTASSIUM CHLORIDE; WATER; SODIUM ACETATE; SODIUM CHLORIDE; TRISODIUM CITRATE DIHYDRATE; SODIUM HYDROXIDE

ImproVue®
Ophthalmic Lubricant Drops

Drug Facts

Active Ingredients

Hypromellose (1.7%)

Purpose

Ophthalmic Lubricant

Indications

- For the temporary relief of burning and irritation due to dryness of the eye.
- For use as a lubricant to prevent further irritation or to relieve dryness of the eye.

Warnings

- For external use only.
- To avoid contamination do not touch tip of container or applicator to any surface.
- Do not reuse. Once opened, discard.

Stop use and ask a doctor if

- If you experience eye pain, changes in vision, continued redness or irritation of the eye, or if the condition worsens or persists for more than 72 hours, discontinue use and consult a doctor.
- If solution changes color or becomes cloudy, do not use.

Keep out of reach of children

- If swallowed, get medical help or contact a Poison Control Center right away.

Directions

- Remove cap from syringe and screw on applicator tip.
- Instill 1 or 2 drops in the affected eye(s) as needed.

Other Information

- Do not use if pouch is damaged or has been previously opened.
- Protect from freezing
- Store at or below 25°C (77°F)

Inactive Ingredients

Calcium chloride dihydrate, hydrochloric acid [May contain one or more of these ingredients for pH adjustment] , magnesium chloride hexahydrate, potassium chloride, purified water, sodium acetate trihydrate, sodium chloride, sodium citrate dihydrate, and sodium hydroxide

Questions or Comments?

(855) 734-2466 or (772) 236-2622 or log onto www.oculussurgical.com

PRINCIPAL DISPLAY PANEL - 6 Pouch Carton

ImproVue®

Ophthalmic Lubricant Drops

- Sterile
- Preservative-free
- Single use, disposable container

Contains:

6 Pouches, each Pouch containing
1 Single Use Syringe, 0.07 fl oz (2 ml)
1 Single Use Applicator Tip

OCULUS®
SURGICAL
www.oculussurgical.com